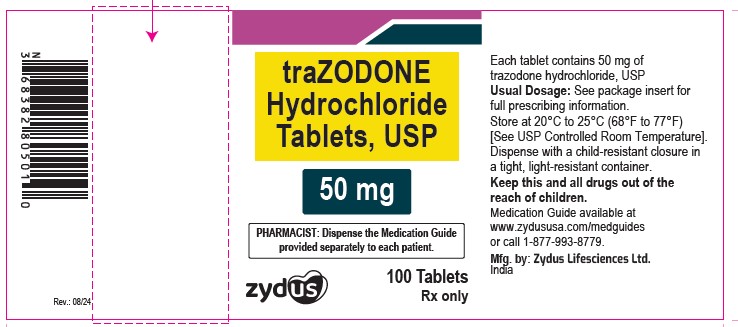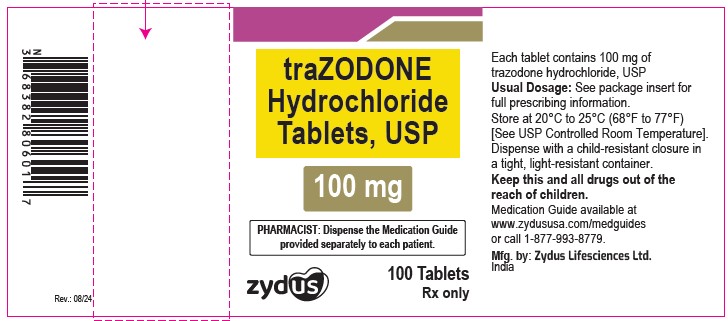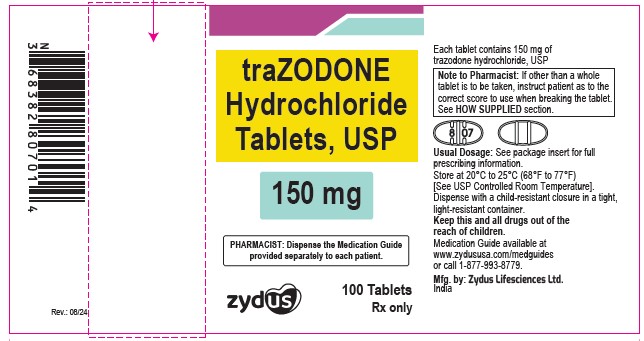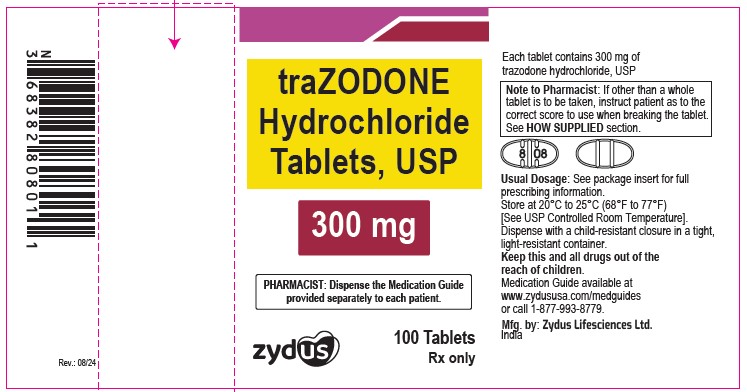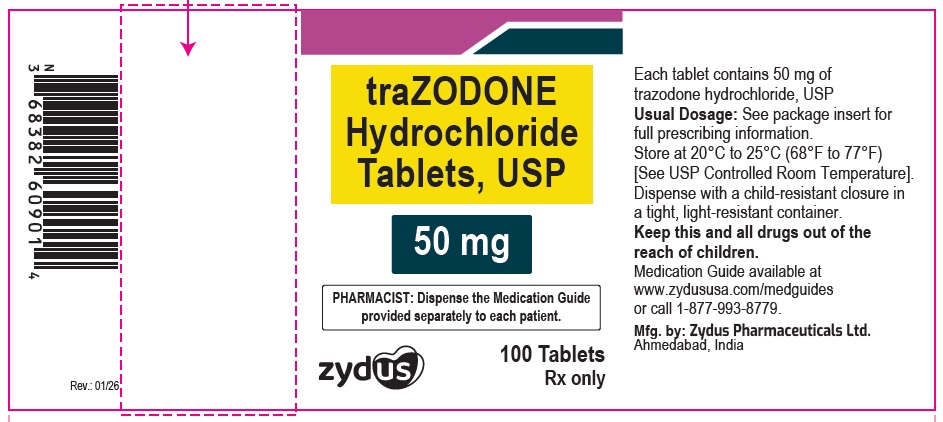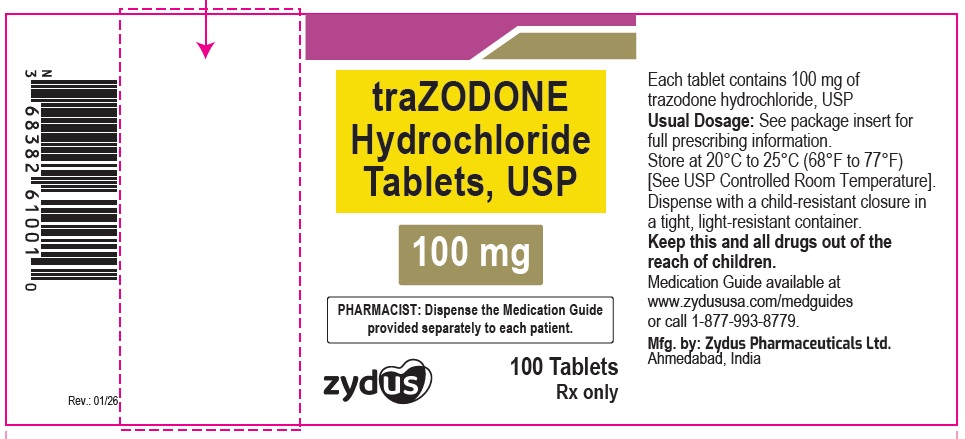 DRUG LABEL: Trazodone Hydrochloride
NDC: 70771-1128 | Form: TABLET
Manufacturer: Zydus Lifesciences Limited
Category: prescription | Type: HUMAN PRESCRIPTION DRUG LABEL
Date: 20260123

ACTIVE INGREDIENTS: TRAZODONE HYDROCHLORIDE 50 mg/1 1
INACTIVE INGREDIENTS: SILICON DIOXIDE; MAGNESIUM STEARATE; CELLULOSE, MICROCRYSTALLINE; STARCH, CORN; SODIUM LAURYL SULFATE; SODIUM STARCH GLYCOLATE TYPE A POTATO

TRAZODONE HYDROCHLORIDE TABLETS

PACKAGE LABEL.PRINCIPAL DISPLAY PANEL

NDC 70771-1128-1

Trazodone Hydrochloride Tablets USP, 50 mg

100 Tablets

Rx only

NDC 70771-1129-1

Trazodone Hydrochloride Tablets USP, 100 mg

100 Tablets

Rx only

NDC 70771-1130-1

Trazodone Hydrochloride Tablets USP, 150 mg

100 Tablets

Rx only

NDC 70771-1131-1

Trazodone Hydrochloride Tablets USP, 300 mg

100 Tablets

Rx only

NDC 70771-1938-1

Trazodone Hydrochloride Tablets USP, 50 mg

100 Tablets

Rx only

NDC 70771-1939-1

Trazodone Hydrochloride Tablets USP, 100 mg

100 Tablets

Rx only